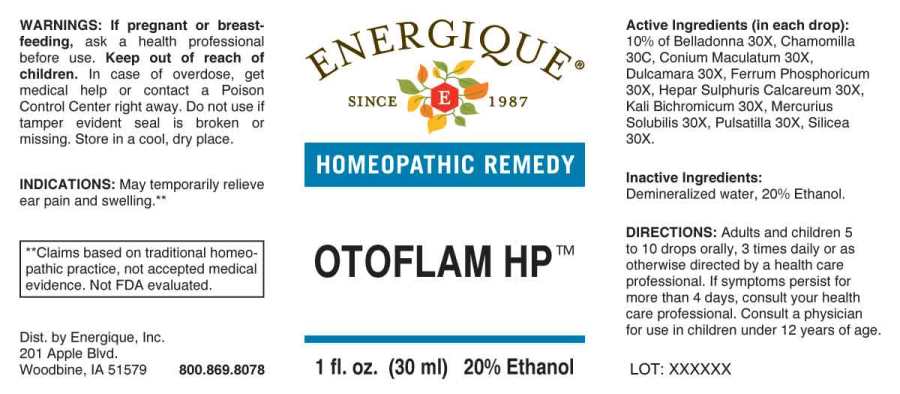 DRUG LABEL: Otoflam
NDC: 44911-0513 | Form: LIQUID
Manufacturer: Energique, Inc.
Category: homeopathic | Type: HUMAN OTC DRUG LABEL
Date: 20241029

ACTIVE INGREDIENTS: ATROPA BELLADONNA WHOLE 30 [hp_X]/1 mL; CONIUM MACULATUM FLOWERING TOP 30 [hp_X]/1 mL; SOLANUM DULCAMARA TOP 30 [hp_X]/1 mL; FERROSOFERRIC PHOSPHATE 30 [hp_X]/1 mL; CALCIUM SULFIDE 30 [hp_X]/1 mL; POTASSIUM DICHROMATE 30 [hp_X]/1 mL; MERCURIUS SOLUBILIS 30 [hp_X]/1 mL; PULSATILLA PRATENSIS WHOLE 30 [hp_X]/1 mL; SILICON DIOXIDE 30 [hp_X]/1 mL; MATRICARIA CHAMOMILLA WHOLE 30 [hp_C]/1 mL
INACTIVE INGREDIENTS: WATER; ALCOHOL

DRUG FACTS:

ACTIVE INGREDIENTS:

(in each drop): 10% of Belladonna 30X, Chamomilla 30C, Conium Maculatum 30X, Dulcamara 30X, Ferrum Phosphoricum 30X, Hepar Sulphuris Calcareum 30X, Kali Bichromicum 30X, Mercurius Solubilis 30X, Pulsatilla 30X, Silicea 30X.

INDICATIONS:

May temporarily relieve ear pain and swelling.**

**Claims based on traditional homeopathic practice, not accepted medical evidence. Not FDA evaluated.

WARNINGS:

If pregnant or breast-feeding, ask a health professional before use.

Keep out of reach of children. In case of overdose, get medical help or contact a Poison Control Center right away.

Do not use if tamper evident seal is broken or missing. Store in a cool, dry place.

Keep out of reach of children. In case of overdose, get medical help or contact a Poison Control Center right away.

DIRECTIONS:

Adults and children 5 to 10 drops orally, 3 times daily or as otherwise directed by a health care professional. If symptoms persist for more than 4 days, consult your health care professional. Consult a physician for use in children under 12 years of age.

INDICATIONS AND USAGE:

May temporarily relieve ear pain and swelling.**

**Claims based on traditional homeopathic practice, not accepted medical evidence. Not FDA evaluated.

INACTIVE INGREDIENTS:

Demineralized water, 20% Ethanol.

QUESTIONS:

Dist. by Energique, Inc.

201 Apple Blvd

Woodbine, IA 51579

800-869-8078

PACKAGE LABEL DISPLAY:

ENERGIQUE

SINCE 1987

HOMEOPATHIC REMEDY

OTOFLAM HP

1 fl. oz. (30 ml)